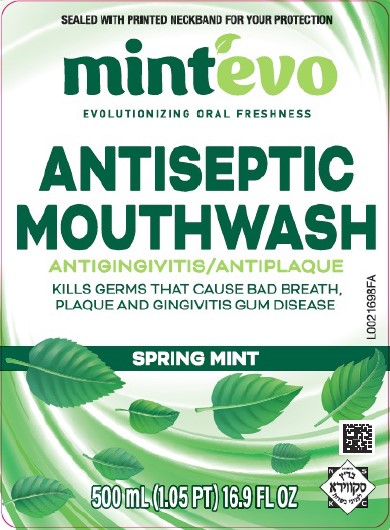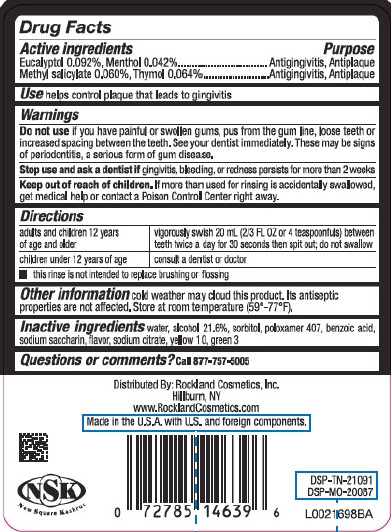 DRUG LABEL: Antiseptic Mouthrinse
NDC: 69892-072 | Form: MOUTHWASH
Manufacturer: Rockland Cosmetics, Inc.
Category: otc | Type: HUMAN OTC DRUG LABEL
Date: 20260206

ACTIVE INGREDIENTS: EUCALYPTOL 0.92 mg/1 mL; MENTHOL 0.42 mg/1 mL; METHYL SALICYLATE 0.6 mg/1 mL; THYMOL 0.64 mg/1 mL
INACTIVE INGREDIENTS: WATER; ALCOHOL; SORBITOL; POLOXAMER 407; BENZOIC ACID; SACCHARIN SODIUM; SODIUM CITRATE; D&C YELLOW NO. 10; FD&C GREEN NO. 3

MINT'EVO 072.003/072AL rev 2-AN
Spring Mint Antiseptic Mouthrinse

Active ingredients

Eucalyptol 0.092%

Menthol 0.042%

Methyl sailcylate 0.060%

Thymol 0.064%

Purpose

Antigingivitis, Antiplaque

Use

Helps control plaque that leads to gingivitis

Warnings

For this product

Do not use if

you have painful or swollen gums, pus from the gum line, loose teeth or increased spacing between the teeth. See your dentist immediately. These may be signs of periodontitis, a serious form of gum disease.

Stop use and ask a dentist if

gingivitis, bleeding, or rednss persists for more than 2 weeks

Keep out of reach of children.

If more than used for rinsing is accidentally swallowed, get medical help or contact a Poison Control Center right away.

Directions

adults and children 12 years of age and older - vigorously swish 20 ml (2/3 FL OZ or 4 teaspoonfuls) between teeth twice a day for 30 seconds then spit out; do not swallow

children under 12 years of age - consult a dentist or doctor

- this rinse is not intended to replace brushing or flossing

Other information

cold weather may cloud this product. Its antiseptic properties are not affected. Store at room temperature (59° -77° F).

Inactive ingredients

water, alcohol 21.6 %, sorbitol solution, flavor, poloxamer 407, benzoic acid, sodium saccharin, sodium citrate, yellow 10, green 3

Questions or comments?

Call 877-757-5005

Adverse reaction

Distributed By: Rockland Cosmetics, Inc.

Hillburn, NY

www.RocklandCosmetics.com

Made in the U.S.A. with U.S. and foreign components.

NSK

New Square Kashrus

DSP-TN-21091

DSP-MO-20087

Principal display panel

SEALED WITH PRINTED NECKBAND FOR YOUR PROTECTION

mint'evo

EVOLUTIONIZING ORAL FRESSNESS

ANTISEPTIC MOUTHWASH

ANTIGINGIVITIS/ANTIPLAQUE

KILLS GERMS THAT CAUSE BAD BREATH, PLAQUE AND GINGIVITIS THE GUM DISEASE

SPRING MINT

500 mL (1.05 PT) 16.9 FL OZ